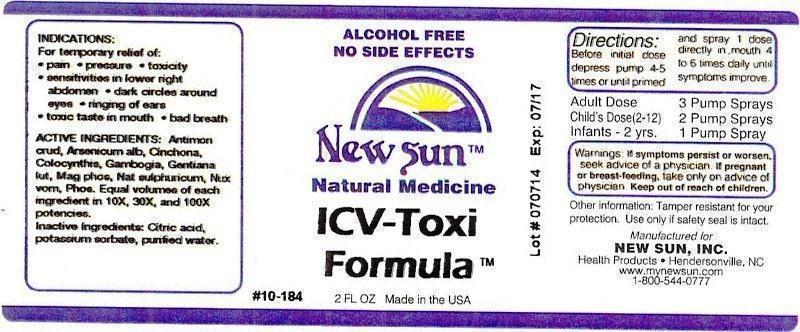 DRUG LABEL: ICV Toxi Formula
NDC: 66579-0056 | Form: LIQUID
Manufacturer: New Sun Inc.
Category: homeopathic | Type: HUMAN OTC DRUG LABEL
Date: 20140905

ACTIVE INGREDIENTS: ANTIMONY TRISULFIDE 10 [hp_X]/59 mL; ARSENIC TRIOXIDE 10 [hp_X]/59 mL; CINCHONA OFFICINALIS BARK 10 [hp_X]/59 mL; CITRULLUS COLOCYNTHIS FRUIT PULP 10 [hp_X]/59 mL; GAMBOGE 10 [hp_X]/59 mL; GENTIANA LUTEA ROOT 10 [hp_X]/59 mL; MAGNESIUM PHOSPHATE, DIBASIC TRIHYDRATE 10 [hp_X]/59 mL; SODIUM SULFATE 10 [hp_X]/59 mL; STRYCHNOS NUX-VOMICA SEED 10 [hp_X]/59 mL; PHOSPHORUS 10 [hp_X]/59 mL
INACTIVE INGREDIENTS: CITRIC ACID MONOHYDRATE; POTASSIUM SORBATE; WATER

ICV-Toxi Formula

DOSAGE AND ADMINISTRATION

Directions: Before initial dose depress pump 4-5 times or until primed and spray 1 dose directly in mouth 4 to 6 times daily until symptoms improve.

Adult Dose: 3 Pump Sprays

Child's Dose (2-12): 2 Pump Sprays

Infants - 2 yrs. 1 Pump Spray

WARNINGS

Warnings: If symptoms persist or worsen, seek advice of a physician. If pregnant or breast-feeding, take only on advice of physician.

Keep out of reach of children.

Other information: Tamper resistant for your protection. Use only if safety seal is intact.

PURPOSE

Indications: For temporary relief of: pain, pressure, toxicity, sensitivities in lower right abdomen, dark circles around eyes, ringing of ears, toxic taste in mouth, bad breath.

ACTIVE INGREDIENT

Active Ingredients: Antimonium crudum, Arsenicum album, Cinchona officinalis, Colocynthis, Gambogia, Gentiana lutea, Magnesia phosphorica, Natrum sulphuricum, Nux vomica, Phosphorus. Equal volumes of each ingredient in 10X, 30X, 100X potencies.

Inactive Ingredient: Citric acid, potassium sorbate, purified water.

Indications: For temporary relief of:

- pain
- pressure
- toxicity
- sensitivities in lower right abdomen
- dark circles around eyes
- ringing of ears
- toxic taste in mouth
- bad breath